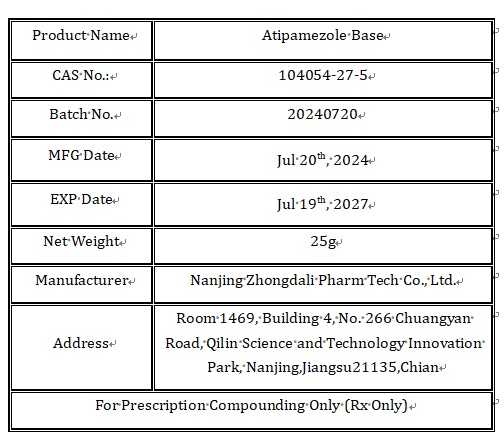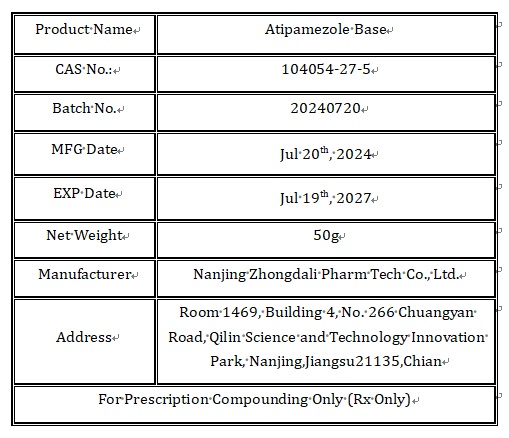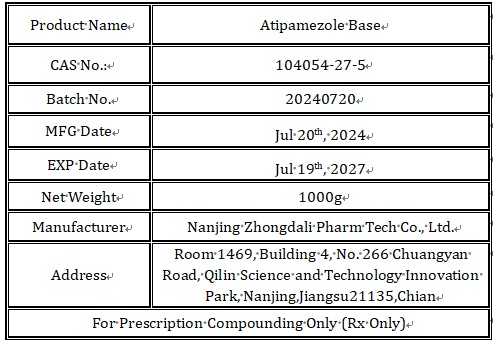 DRUG LABEL: Atipamezole Base
NDC: 86225-001 | Form: POWDER
Manufacturer: Nanjing Zhongdali Pharm Tech Co., Ltd.
Category: other | Type: BULK INGREDIENT - ANIMAL DRUG
Date: 20250428

ACTIVE INGREDIENTS: ATIPAMEZOLE 1 g/1 g

86225-001